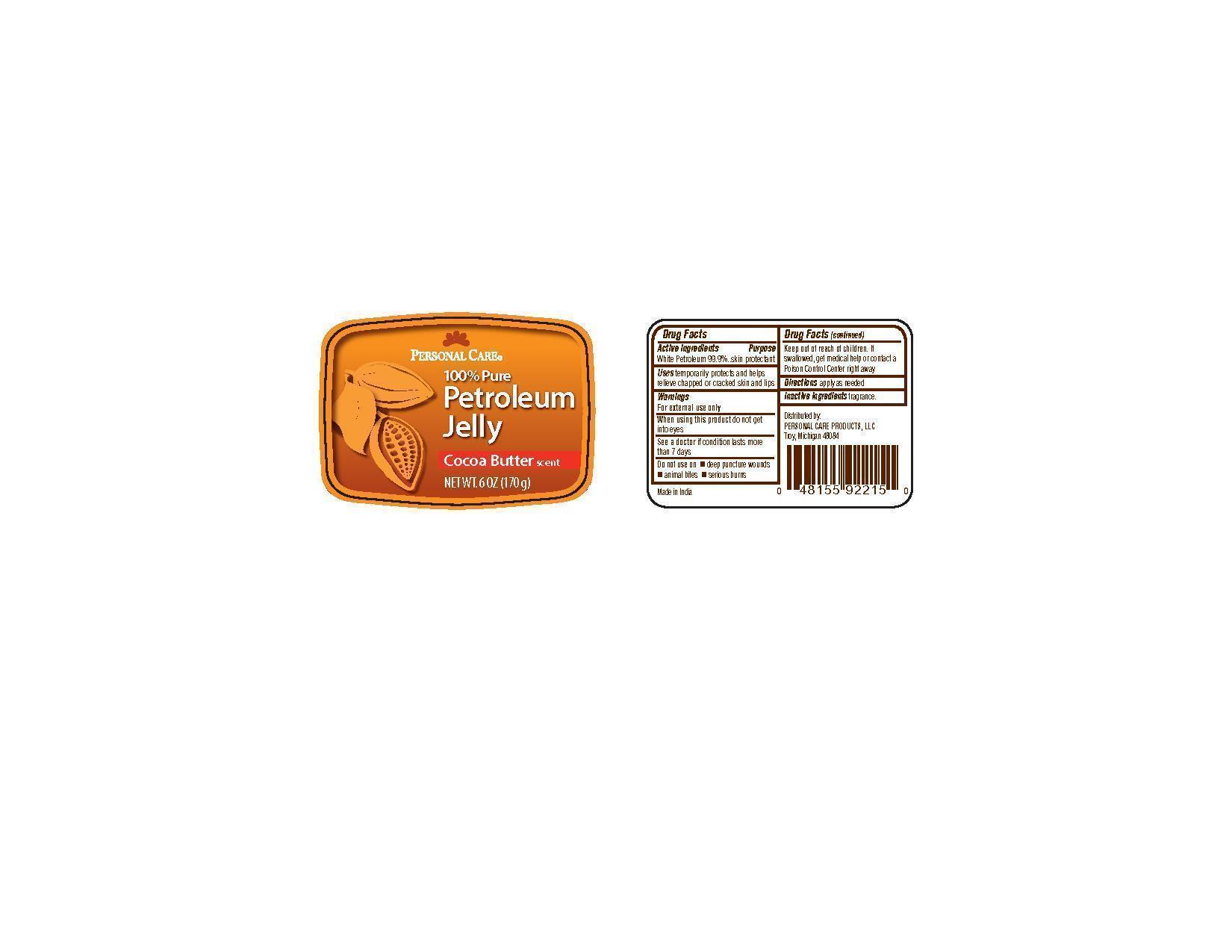 DRUG LABEL: Personal Care Products petroleum
                
                
NDC: 29500-8050 | Form: JELLY
Manufacturer: Personal Care Products
Category: otc | Type: HUMAN OTC DRUG LABEL
Date: 20120629

ACTIVE INGREDIENTS: PETROLATUM 1 g/1 g

Personal Care Petroleum

Active ingredients

White petroleum jelly 99.9%

Purpose skin protectant

Keep out of reach of children. If swallowed, get medical help or contact a Poison Control Center right away.

INDICATIONS AND USAGE

Uses temporarily protects and helps relieve chapped or cracked skin and lips

Warnings

For external use only

When using this product do not get into eyes

See a doctor if condition lasts more than 7 days

Do not use on deep puncture wounds, animal bites, serious burns

DOSAGE AND ADMINISTRATION

Directions apply as needed

Inactive ingredients fragrance

PACKAGE LABEL

Personal Care
100% Petroleum Jelly
Cocoa Butter scent
Net wt. 6 oz (170 g)
Distributed by:
Personal Care Products, LLC
Troy, Michigan 48084
Made in India